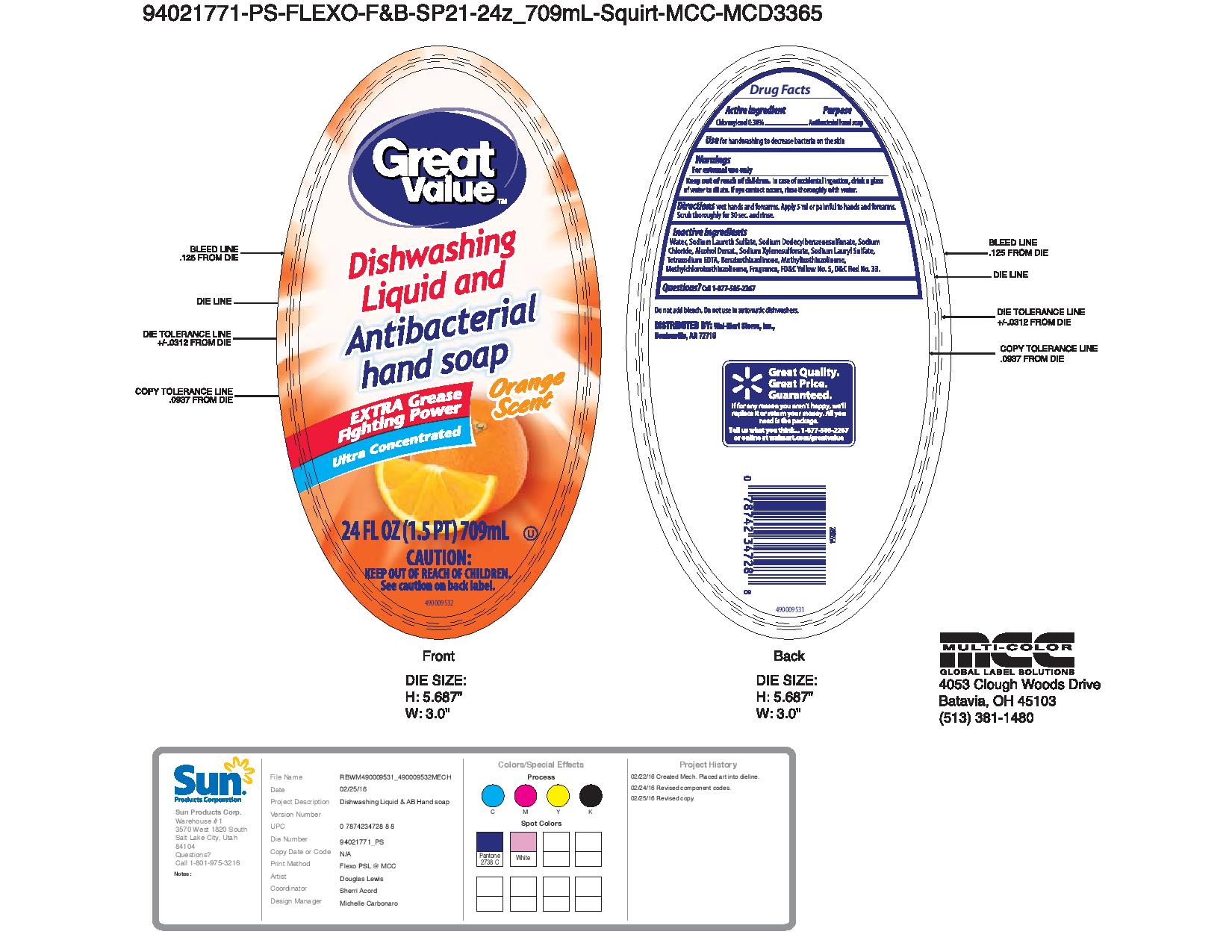 DRUG LABEL: Great Value Orange Scent
NDC: 63691-033 | Form: SOAP
Manufacturer: Sun Products Corporation
Category: otc | Type: HUMAN OTC DRUG LABEL
Date: 20170307

ACTIVE INGREDIENTS: CHLOROXYLENOL 0.3 g/100 mL
INACTIVE INGREDIENTS: METHYLCHLOROISOTHIAZOLINONE; FD&C YELLOW NO. 5; SODIUM CHLORIDE; WATER; SODIUM LAURETH SULFATE; D&C RED NO. 33; EDETATE SODIUM; ALCOHOL; BENZISOTHIAZOLINONE; SODIUM XYLENESULFONATE; SODIUM LAURYL SULFATE; METHYLISOTHIAZOLINONE; SODIUM DODECYLBENZENESULFONATE

Active ingredient

Chloroxylenol 0.30%

INDICATIONS AND USAGE

Use helps fight germs on hands when used as a hand soap

WARNINGS

For external use only

Keep out of reach of children. In case of accidental ingestion, drink a glass of water to dilute. If eye contact occurs, rinse thoroughly with water.

DOSAGE AND ADMINISTRATION

Directions wet hands and forearms. Apply 5 mL or palmful to hands and forearms. Scrub thoroughly for 30 sec. and rinse.

PURPOSE

Dishwashing Liquid and Antibacterial hand soap

INACTIVE INGREDIENT

Inactive ingredients Water, Sodium Laureth Sulfate, Sodium Dodecylbenzenesulfonate, Sodium Chloride, Alcohol Denat., Sodium Xylenesulfonate, Sodium Lauryl Sulfate, Tetrasodium EDTA, Benzisothiazolinone, Methylisothiazolinone, Methylchloroisothiazolinone, Fragrance, FD&C Yellow No. 5, D&C Red No. 33

Questions? 1-877-505-2267

PACKAGE LABEL

LBLFR

LBLBK

RBWM490009531_490009532MECH LBL FR LBL BK-page-001.jpg